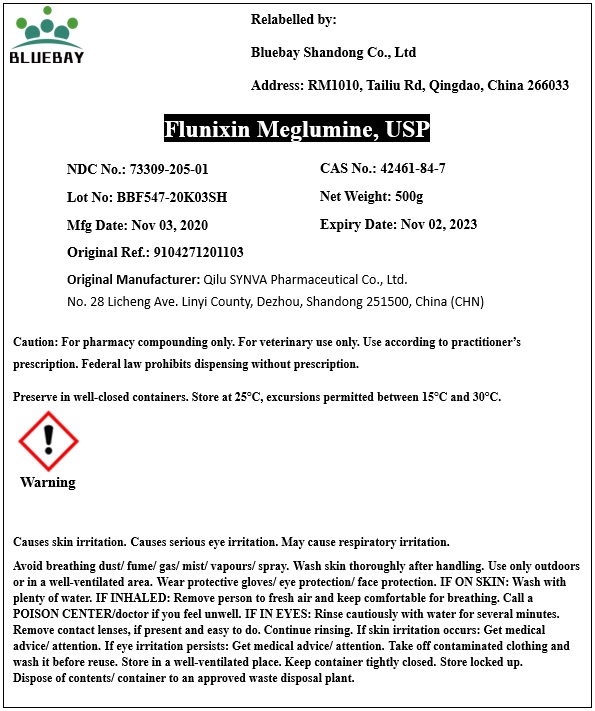 DRUG LABEL: Flunixin Meglumine
NDC: 73309-205 | Form: POWDER
Manufacturer: BLUEBAY SHANDONG CO.,LTD
Category: other | Type: BULK INGREDIENT
Date: 20201217

ACTIVE INGREDIENTS: Flunixin Meglumine 1 g/1 g

Flunixin Meglumine